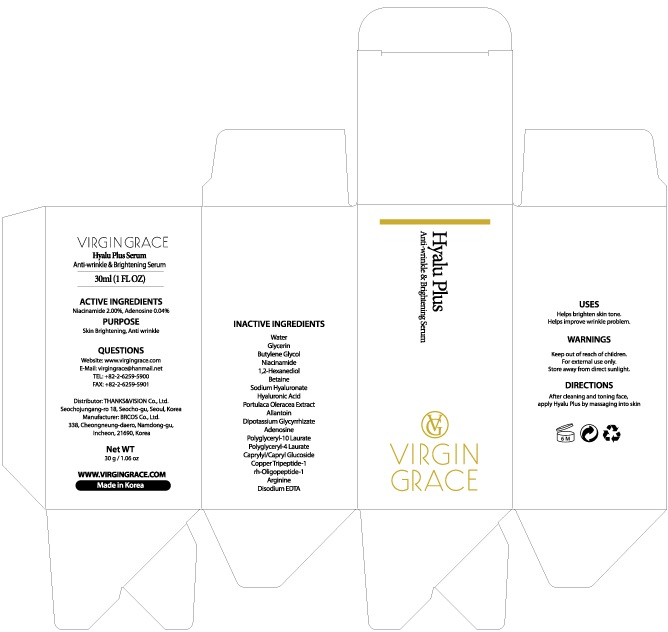 DRUG LABEL: VIRGIN GRACE Hyalu Plus Serum
NDC: 73340-020 | Form: LIQUID
Manufacturer: Thanks & Vision Co., Ltd.
Category: otc | Type: HUMAN OTC DRUG LABEL
Date: 20190917

ACTIVE INGREDIENTS: Niacinamide 0.60 g/30 mL; Adenosine 0.01 g/30 mL
INACTIVE INGREDIENTS: Water; Glycerin

ACTIVE INGREDIENT

Active Ingredient: Niacinamide 2.00%, Adenosine 0.04%

INACTIVE INGREDIENT

Inactive Ingredients:

Water, Glycerin, Butylene Glycol, 1,2-Hexanediol, Betaine, Sodium Hyaluronate, Hyaluronic Acid, Portulaca Oleracea Extract, Allantoin, Dipotassium Glycyrrhizate, Polyglyceryl-10 Laurate, Polyglyceryl-4 Laurate, Caprylyl/Capryl Glucoside, Copper Tripeptide-1, rh-Oligopeptide-1, Arginine, Disodium EDTA

PURPOSE

Purpose: Skin Brightening, Anti wrinkle

WARNINGS

Keep out of reach of children.
For external use only.
Store away from direct sunlight.

KEEP OUT OF REACH OF CHILDREN

Uses

Helps brighten skin tone.
Helps improve wrinkle problem.

Directions

After cleaning and toning face, apply Hyalu Plus by massaging into skin